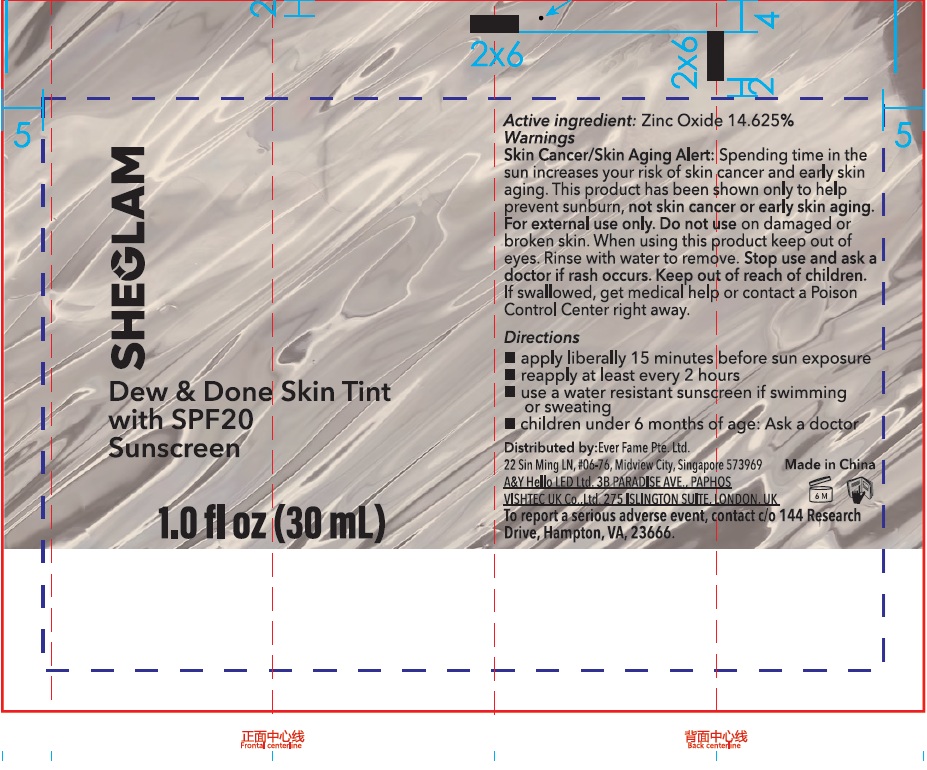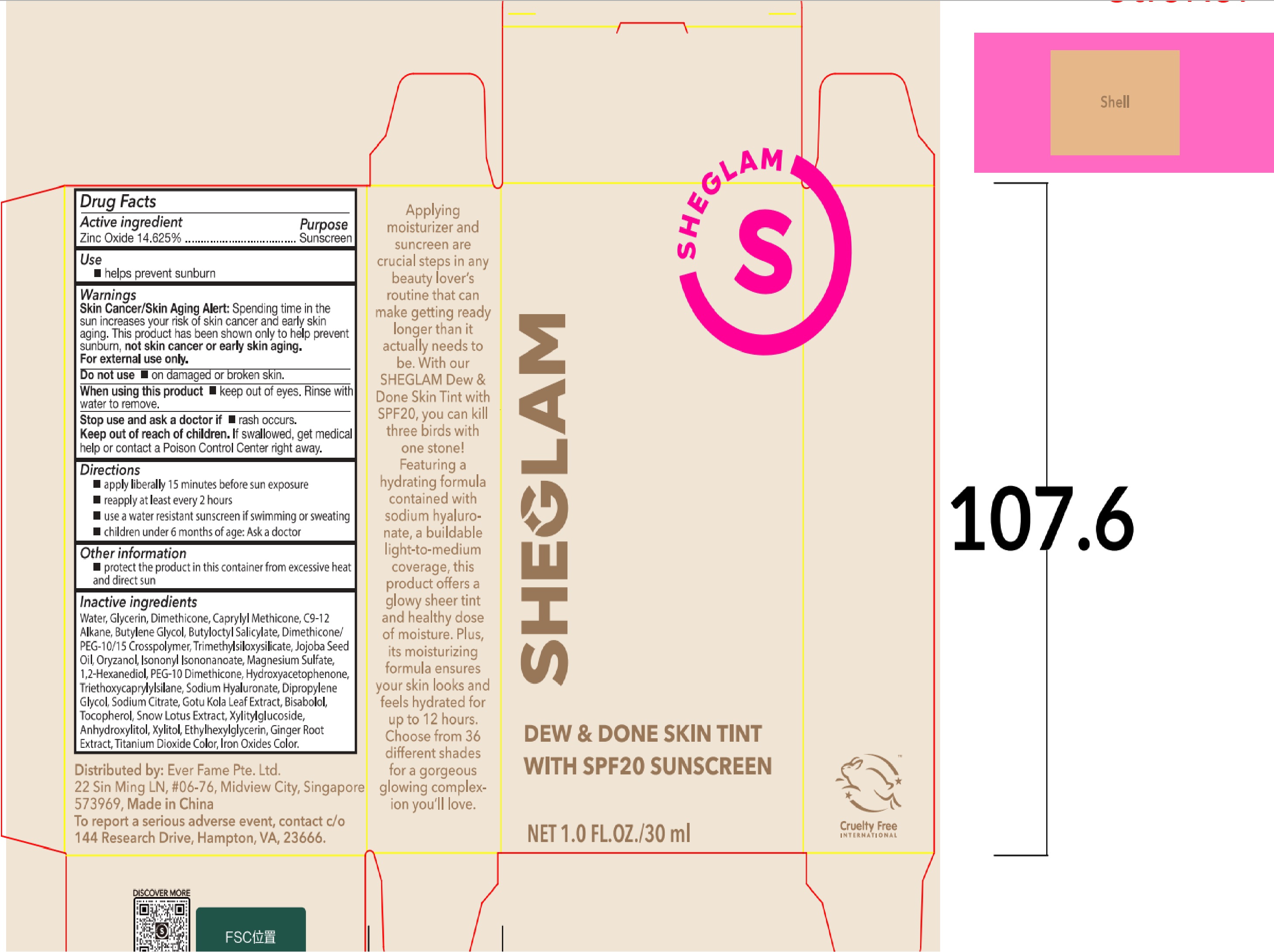 DRUG LABEL: Sheglam Dew and Done Skin Tint with SPF 20 Shell
NDC: 85068-031 | Form: CREAM
Manufacturer: EVER FAME PTE. LTD.
Category: otc | Type: HUMAN OTC DRUG LABEL
Date: 20250113

ACTIVE INGREDIENTS: ZINC OXIDE 146.25 mg/1 mL
INACTIVE INGREDIENTS: WATER; GLYCERIN; DIMETHICONE; CAPRYLYL METHICONE; C9-12 ALKANE; BUTYLENE GLYCOL; BUTYLOCTYL SALICYLATE; DIMETHICONE/PEG-10/15 CROSSPOLYMER; JOJOBA OIL; ORYZANOL; ISONONYL ISONONANOATE; MAGNESIUM SULFATE; 1,2-HEXANEDIOL; HYDROXYACETOPHENONE; TRIETHOXYCAPRYLYLSILANE; SODIUM HYALURONATE; DIPROPYLENE GLYCOL; SODIUM CITRATE; BISABOLOL; TOCOPHEROL; XYLITYLGLUCOSIDE; ANHYDROXYLITOL; XYLITOL; ETHYLHEXYLGLYCERIN; GINGER; TITANIUM DIOXIDE; FERRIC OXIDE RED

Sheglam Dew & Done Skin Tint with SPF 20, Shell

Active ingredient

Zinc Oxide 14.625%

Purpose

Sunscreen

Use

- helps prevent sunburn

Warnings

Skin Cancer/Skin Aging Alert:Spending time in the sun increases your risk of skin cancer and early skin aging. This product has been shown only to help prevent sunburn, not skin cancer or early skin aging.

For external use only.

Do not use

- on damaged or broken skin.

When using this product

- keep out of eyes. Rinse with water to remove.

Stop use and ask a doctor if

- rash occurs.

Keep out of reach of children.

If swallowed, get medical help or contact a Poison Control Center right away.

Directions

- apply liberally 15 minutes before sun exposure
- reapply at least every 2 hours
- use a water resistant sunscreen if swimming or sweating
- children under 6 months of age: Ask a doctor

Other information

- protect the product in this container from excessive heat and direct sun

Inactive ingredients

Water, Glycerin, Dimethicone, Caprylyl Methicone, C9-12 Alkane, Butylene Glycol, Butyloctyl Salicylate, Dimethicone/PEG-10/15 Crosspolymer, Trimethylsiloxysilicate, Jojoba Seed Oil, Oryzanol, Isononyl Isononanoate, Magnesium Sulfate, 1,2-Hexanediol, PEG-10 Dimethicone, Hydroxyacetophenone, Triethoxycaprylylsilane, Sodium Hyaluronate, Dipropylene Glycol, Sodium Citrate, Gotu Kola Leaf Extract, Bisabolol, Tocopherol, Snow Lotus Extract, Xylitylglucoside, Anhydroxylitol, Xylitol, Ethylhexylglycerin, Ginger Root Extract, Titanium Dioxide Color, Iron Oxides Color.